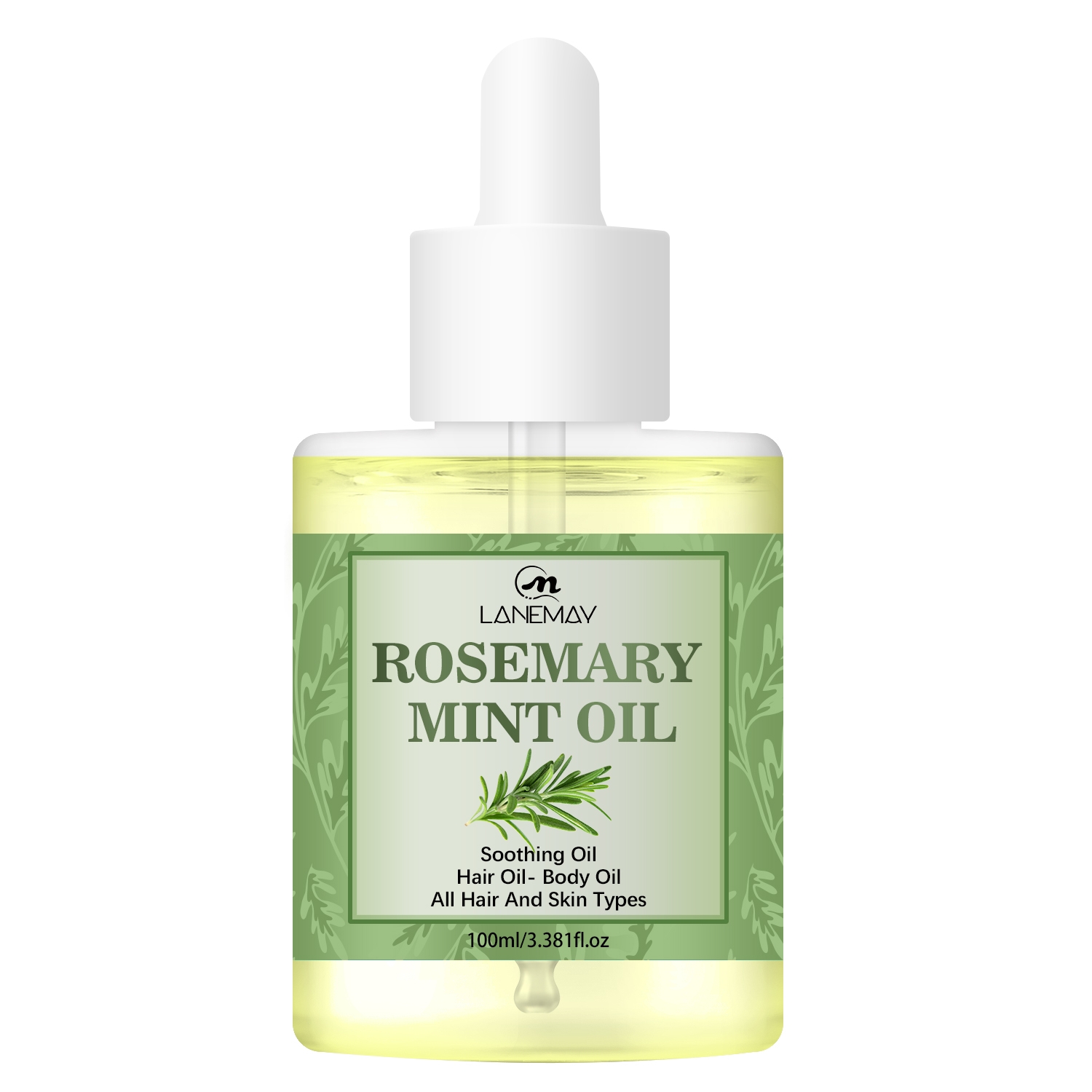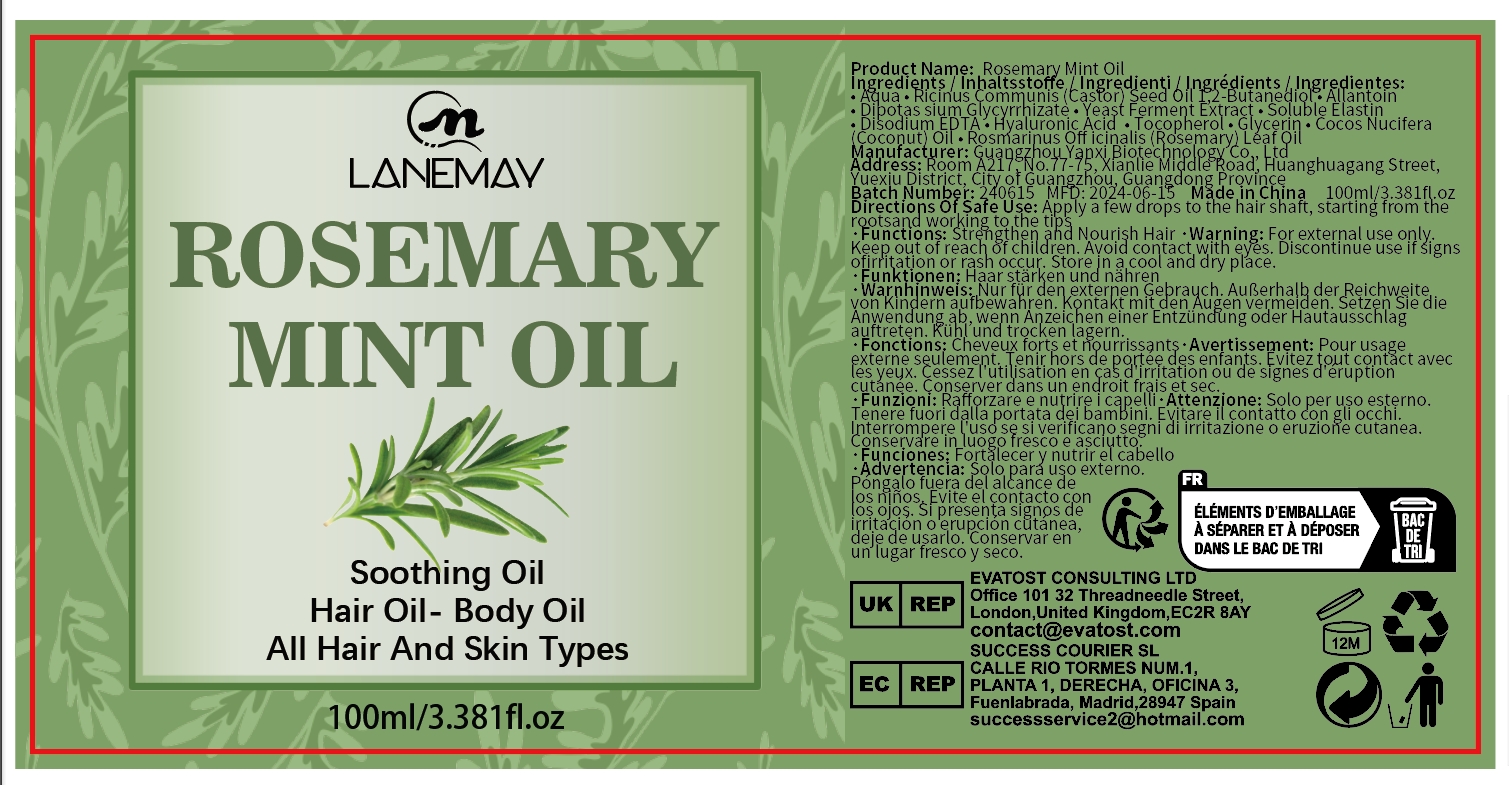 DRUG LABEL: Rosemary Mint Oil
NDC: 84025-076 | Form: OIL
Manufacturer: Guangzhou Yanxi Biotechnology Co.. Ltd
Category: otc | Type: HUMAN OTC DRUG LABEL
Date: 20240720

ACTIVE INGREDIENTS: HYALURONIC ACID 3 mg/100 mL; ALLANTOIN 5 mg/100 mL
INACTIVE INGREDIENTS: WATER

DOSAGE AND ADMINISTRATION

Nourishes scalp

WARNINGS

keep out of children

INACTIVE INGREDIENT

Aqua

INDICATIONS AND USAGE

Nourishes scalp and skin

keep out of children

PURPOSE

Nourishes and moisturizes scalp and skin